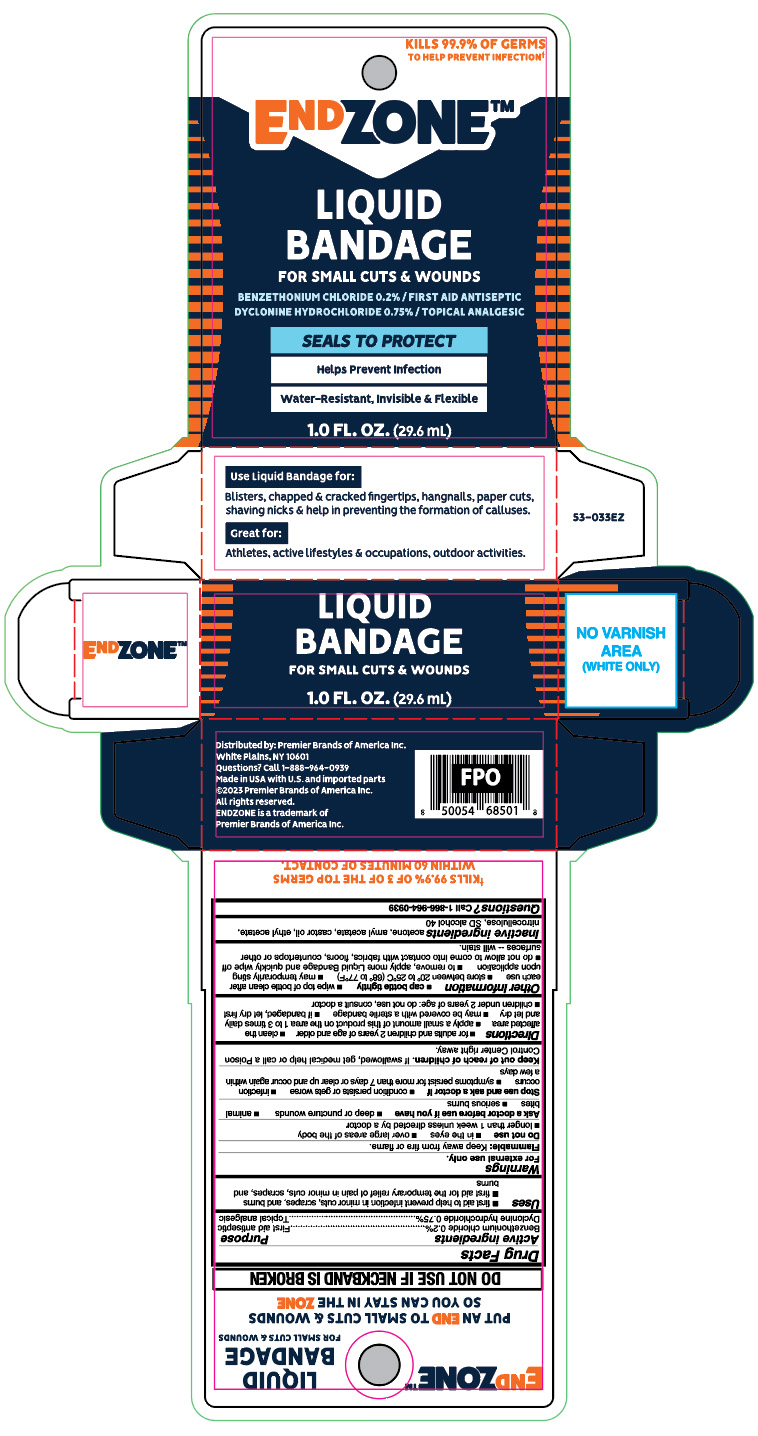 DRUG LABEL: Liquid Bandage
NDC: 56104-502 | Form: LIQUID
Manufacturer: Premier Brands of America Inc.
Category: otc | Type: HUMAN OTC DRUG LABEL
Date: 20251007

ACTIVE INGREDIENTS: BENZETHONIUM CHLORIDE 2 mg/1 mL; DYCLONINE HYDROCHLORIDE 7.5 mg/1 mL
INACTIVE INGREDIENTS: AMYL ACETATE; CASTOR OIL; ETHYL ACETATE; PYROXYLIN; ALCOHOL; ACETONE

Endzone Liquid Bandage

Active ingredients

Benzethonium chloride 0.2%
Dyclonine hydrochloride 0.75%

Purpose

First aid antiseptic
Topical analgesic

Uses

- first aid to help prevent infection in minor cuts, scrapes, and burns
- first aid for the temporary relief of pain in minor cuts, scrapes, and burns

Warnings

For external use only.

Flammable:

Keep away from fire or flame.

Do not use

- in the eyes
- over large areas of the body
- longer than 1 week unless directed by a doctor

Ask a doctor before use if you have

- deep or puncture wounds
- animal bites
- serious burns

Stop use and ask a doctor if

- conditions persists or gets worse
- infection occurs
- symptoms persist for than 7 days or clear up and occur again within a few days

Keep out of reach of children.

If swallowed, get medical help or call a Poison Control Center right away.

Directions

- for adults and children 2 years of age and older
- clean affected area
- apply a small amount on the area 1 to 3 times daily and let dry
- may be covered with a sterile bandage
- if bandaged, let dry first
- children under under 2 years of age; do not sure, consult a doctor

Other information

- cap bottle tightly
- store between 20° to 25°C (68° to 77°F)
- may temporarily sting upon application
- to remove, apply more Liquid Bandage and quickly wipe off
- do not allow to come into contact with fabrics, floors, countertops or other surfaces - will stain

Inactive ingredients

acetone, amyl acetate, castor oil, ethyl acetate, nitrocellulose, SD slcohol 40

Questions

Call 1-866-964-0939

Principal Display Panel

KILLS 99.9% OF GERMS

TO HELP PREVENT INFECTION

EndZone

LIQUID

BANDAGE

FOR SMALL CUTS & WOUNDS

BENZETHONIUM CHLORIDE 0.2%/FIRST AID ANTISEPTIC

DYCLONINE HYDROCHLORIDE 0.75%/TOPICAL ANALGESIC

SEALS TO PROTECT

Helps Prevent Infection

Water-Resistant, Invisible & Flexible

1.0 FL OZ (29.6 mL)